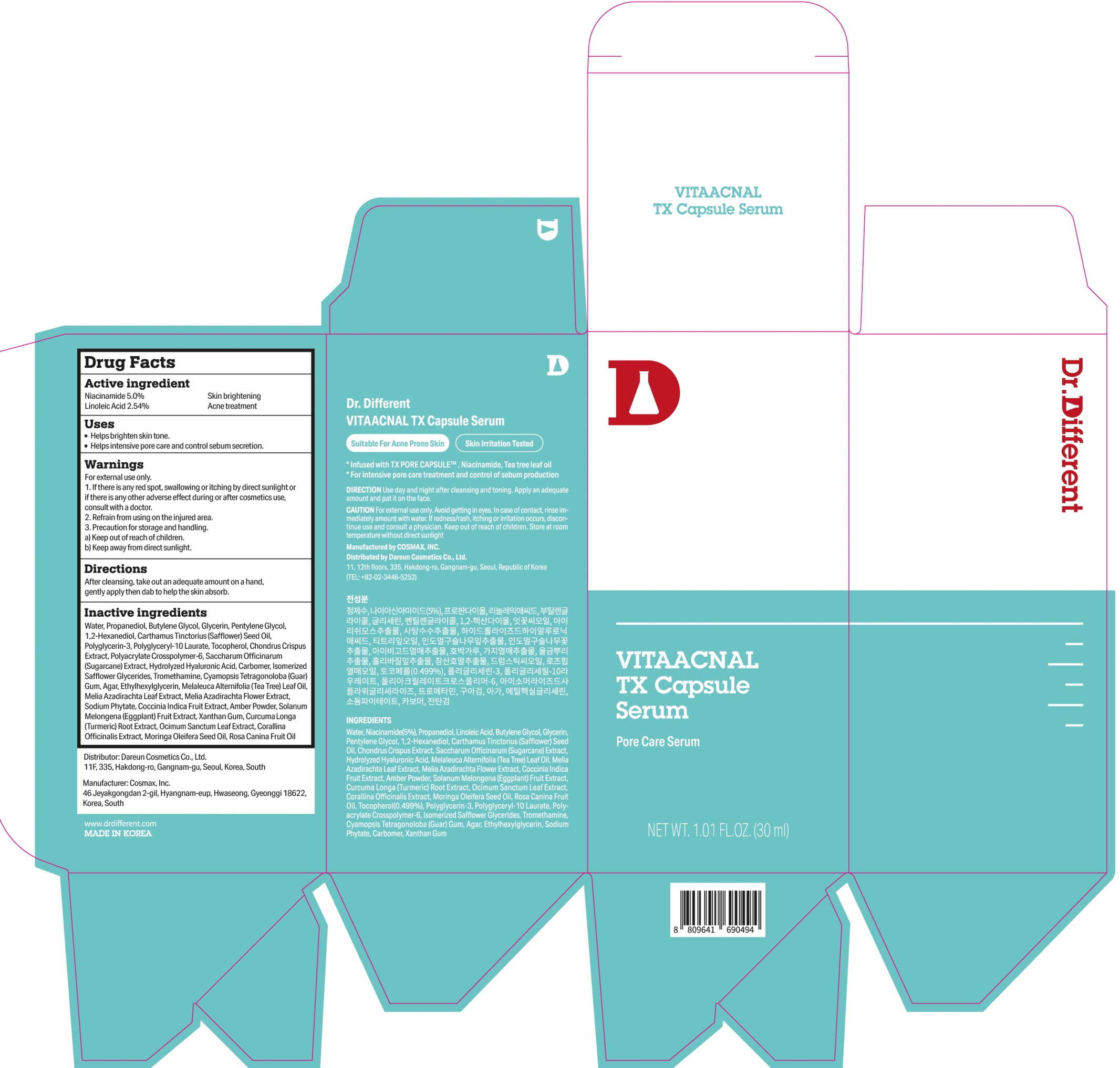 DRUG LABEL: Dr.Different VITAACNAL TX Capsule Serum
NDC: 81710-110 | Form: LIQUID
Manufacturer: Dareun Cosmetics Co., Ltd.
Category: otc | Type: HUMAN OTC DRUG LABEL
Date: 20211214

ACTIVE INGREDIENTS: Niacinamide 1.5 g/30 mL; Linoleic Acid 0.76 g/30 mL
INACTIVE INGREDIENTS: WATER; Propanediol; Butylene Glycol; Glycerin

ACTIVE INGREDIENTS

Niacinamide 5.0%
Linoleic Acid 2.54%

INACTIVE INGREDIENTS

Water, Propanediol, Butylene Glycol, Glycerin, Pentylene Glycol, 1,2-Hexanediol, Carthamus Tinctorius (Safflower) Seed Oil, Polyglycerin-3, Polyglyceryl-10 Laurate, Tocopherol, Chondrus Crispus Extract, Polyacrylate Crosspolymer-6, Saccharum Officinarum (Sugarcane) Extract, Hydrolyzed Hyaluronic Acid, Carbomer, Isomerized Safflower Glycerides, Tromethamine, Cyamopsis Tetragonoloba (Guar) Gum, Agar, Ethylhexylglycerin, Melaleuca Alternifolia (Tea Tree) Leaf Oil, Melia Azadirachta Leaf Extract, Melia Azadirachta Flower Extract, Sodium Phytate, Coccinia Indica Fruit Extract, Amber Powder, Solanum Melongena (Eggplant) Fruit Extract, Xanthan Gum, Curcuma Longa (Turmeric) Root Extract, Ocimum Sanctum Leaf Extract, Corallina Officinalis Extract, Moringa Oleifera Seed Oil, Rosa Canina Fruit Oil

PURPOSE

Skin brightening
Acne treatment

WARNINGS

For external use only.
1. If there is any red spot, swallowing or itching by direct sunlight or if there is any other adverse effect during or after cosmetics use, consult with a doctor.
2. Refrain from using on the injured area.
3. Precaution for storage and handling.
a) Keep out of reach of children.
b) Keep away from direct sunlight.

KEEP OUT OF REACH OF CHILDREN

Uses

■ Helps brighten skin tone.
■ Helps intensive pore care and control sebum secretion.

Directions

After cleansing, take out an adequate amount on a hand, gently apply then dab to help the skin absorb.